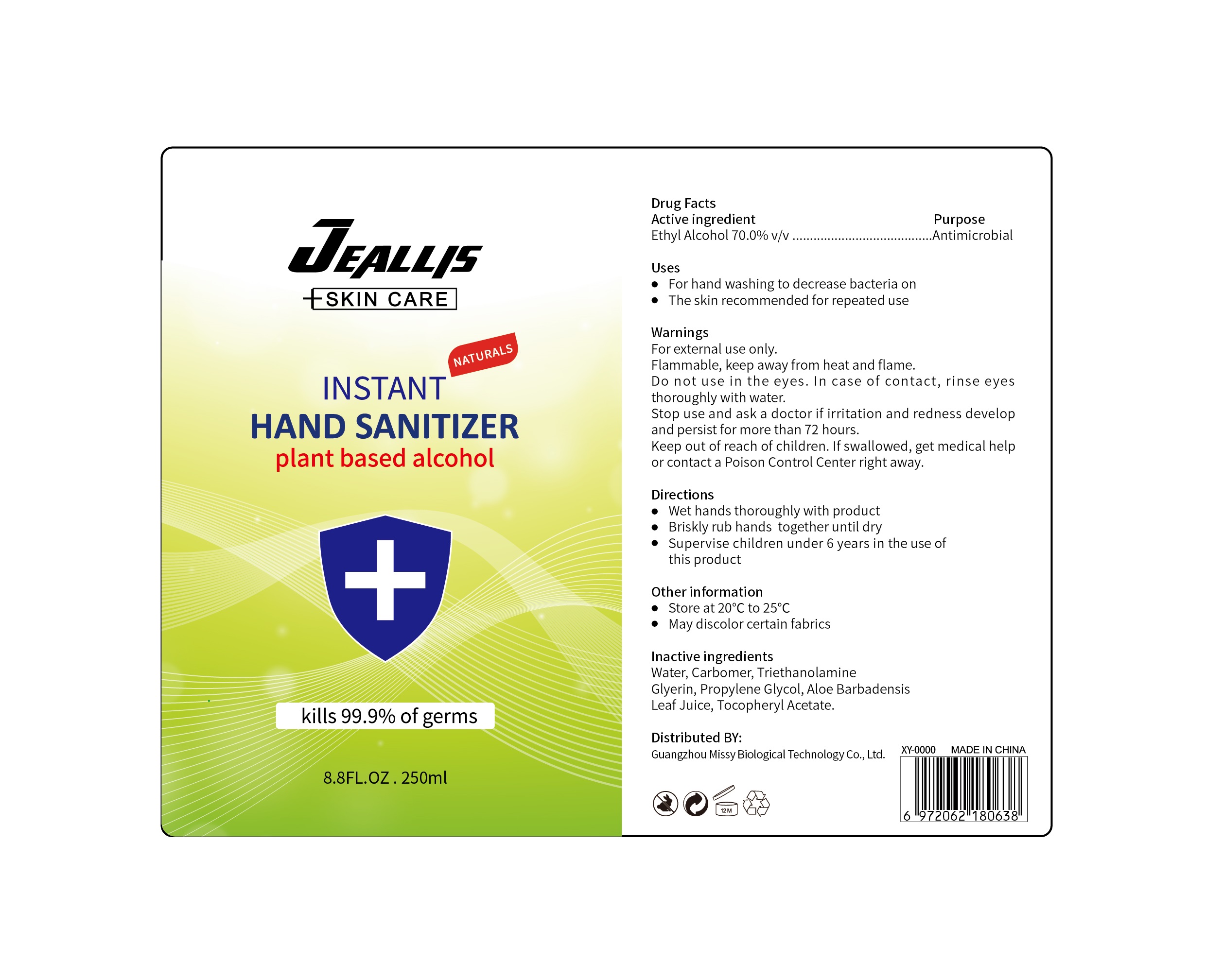 DRUG LABEL: Hand Sanitizer
NDC: 78098-003 | Form: GEL
Manufacturer: GUANGZHOU NODA PHARMACEUTICAL TECHNOLOGY INCORPORATED CO., LTD
Category: otc | Type: HUMAN OTC DRUG LABEL
Date: 20200519

ACTIVE INGREDIENTS: ALCOHOL 70 mL/100 mL
INACTIVE INGREDIENTS: ALPHA-TOCOPHEROL ACETATE 0.5 mL/100 mL; GLYCERIN 2 mL/100 mL; CARBOMER COPOLYMER TYPE A 0.4 mL/100 mL; WATER; TROLAMINE 0.4 mL/100 mL; PROPYLENE GLYCOL 0.5 mL/100 mL; ALOE VERA LEAF 2 mL/100 mL

JEALLIS Hand Sanitizer

Water 24.2%, Alcohol Carbomer 0.4%, Triethanolamine 0.4%, Glycerin 2%, Propylene Glycol 0.5%

,Aloe Barbadensis Leaf Juice 2%, Tocopheryl Acetate 0.5%

Active Ingredient(s)

Ethyl Alcohol 70.0%
Purpose: Antimicrobial

Purpose

Antiseptic, Hand Sanitizer

Use

To decrease bacteria on the skin. Recommended for repeated use.

Warnings

For external use only. Flammable. Keep away from heat or flame

Do not use

- in children less than 2 months of age
- on open skin wounds

When using this product keep out of eyes, ears, and mouth. In case of contact with eyes, rinse eyes thoroughly with water.
Stop use and ask a doctor if irritation or rash occurs. These may be signs of a serious condition.
Keep out of reach of children. If swallowed, get medical help or contact a Poison Control Center right away.

Stop use and ask a doctor if irritation or rash occurs. These may be signs of a serious condition.

Keep out of reach of children. If swallowed, get medical help or contact a Poison Control Center right away.

Directions

- Place enough product on hands to cover all surfaces. Rub hands together until dry.
- Supervise children under 6 years of age when using this product to avoid swallowing.

Other information

- Store between 15-30C (59-86F)
- Avoid freezing and excessive heat above 40C (104F)

Inactive ingredients

glycerin, hydrogen peroxide, purified water USP

Package Label - Principal Display Panel

250 mL NDC: 78098-001-03